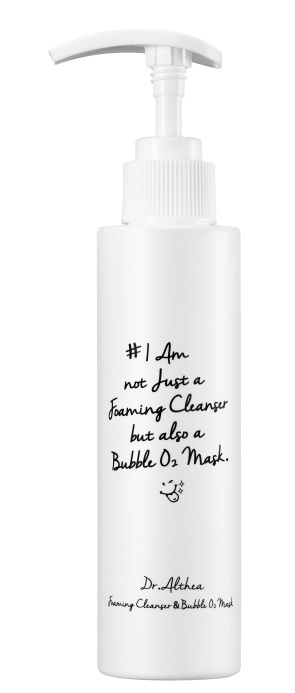 DRUG LABEL: Dr. Althea Foaming Cleanser and Bubble O2 Mask
NDC: 70905-0008 | Form: GEL
Manufacturer: Dr. Althea
Category: otc | Type: HUMAN OTC DRUG LABEL
Date: 20160911

ACTIVE INGREDIENTS: GLYCERIN 0.57 g/100 mL
INACTIVE INGREDIENTS: WATER; BUTYLENE GLYCOL; 1,2-HEXANEDIOL

Drug Facts

ACTIVE INGREDIENT

Glycerin

INACTIVE INGREDIENT

Water, Ammonium Lauryl Sulfate, Acrylates Copolymer, CocamidopropylBetaine , PEG-8 , Cocamide DEA，Methyl Perfluorobutyle Ether, Methyl Perfluoroisobutyl Ether，Olive Oil PEG-7 Esters , Chlorphenesin , Glycerin , Agar, Triethanolamine , Phenoxyethanol , Lithium Magnesium Sodium Silicate , Caprylyl Glycol , Natto Gum, LiliumCandidum Flower Extract , Trehalose , PEG/PPG-20/22 Butyl Ether Dimethicone , 1,2-Hexanediol , Propanediol , Disodium EDTA , Fragrance , Methyl Methacrylate Crosspolymer , Butylene Glycol, Swiftlet Nest Extract , IlliciumVerum (Anise) Fruit Extract , Hydrolyzed Collagen , ArganiaSpinosa Kernel Oil , MesembryanthemumCrystallium Extract，MicrocitrusAustralasica Fruit Extract， CaulerpaLentillifera Extract , Bromelain , Galactomyces Ferment Filtrate , Milk Protein Extract , TremellafuciformisSporocarp Extract , AcerSaccharum (Sugar Maple) Extract , Citrus AurantiumDulcis (Orange) Fruit Extract , VacciniumMyrtillus Fruit/Leaf Extract , SaccharumOfficinarum (Sugar Cane) Extract , Citrus MedicaLimonum(Lemon) Fruit Oil , PortulacaOleracea Extract , Aloe Barbadensis Leaf Juice

PURPOSE

- Deap Cleansing
- Moisturizing

keep out of reach of the children

INDICATIONS AND USAGE

1. Melt down the makeup residues by rolling as if massaging the soft jelly according to the skin texture after putting a proper amount of product on the face without water.
2. Do the final cleansing with plentiful cushion bubbles and wash off clearly with the tepid water.

(You don’t need to use the separate cleanser or soap.)

WARNINGS

1. If the following symptoms occur after product use, stop using the product immediately and consult a dermatologist (continuous use can exacerbate the symptoms).
1) Occurrence of red spots, swelling, itchiness, and other skin irritation
2) If the symptoms above occur after the application area is exposed to direct sunlight
2. Do not use on open wounds, eczema, and other skin irritations
3. Precaution for Storage and Handling
1) Close the lid after use
2) Keep out of reach of infants and children
3) Do not to store in a place with high/low temperature and exposed to direct sunlight
4. Prevent the grains from entering your eyes during use.
5. Close your eyes during rinse for the product not to enter your eyes.
6. When grains entered your eyes, don’t rub your eyes but wash off by water. When they remain as they are, see a specialist for consultation.

DOSAGE AND ADMINISTRATION

for external use only